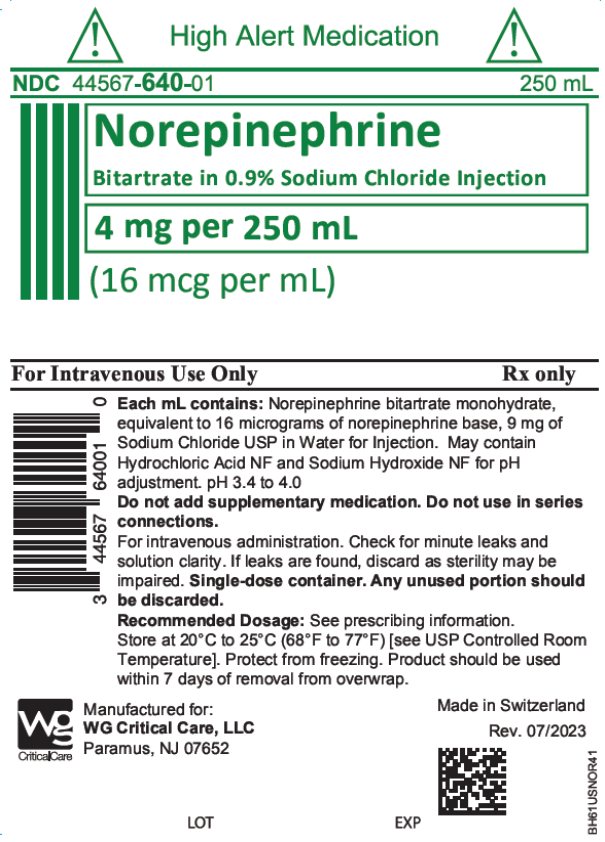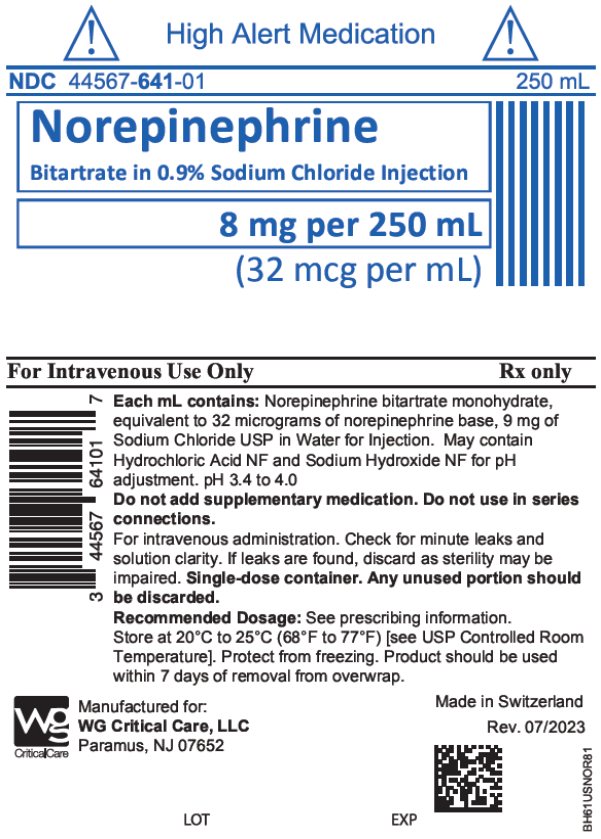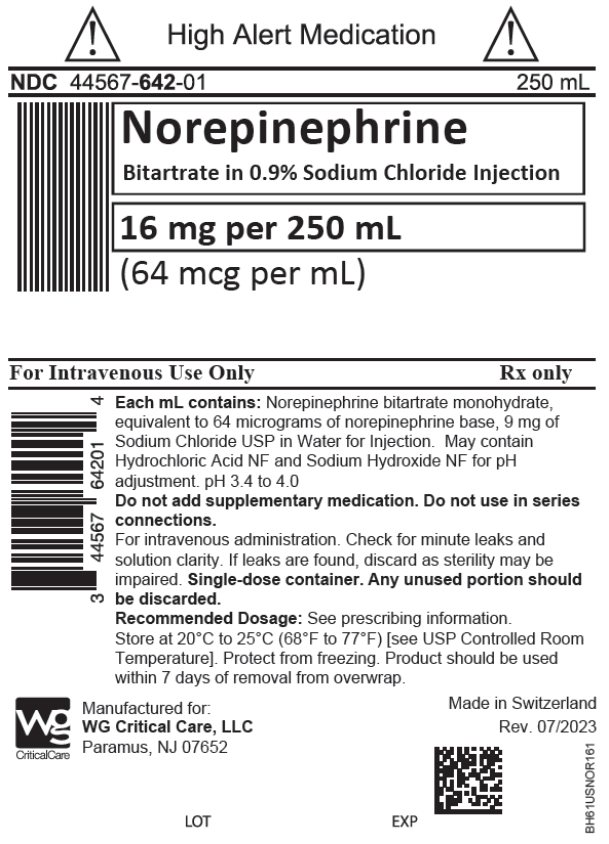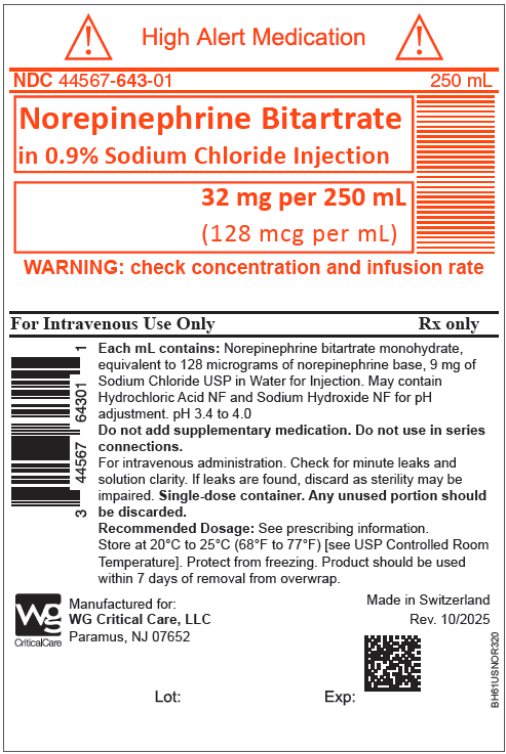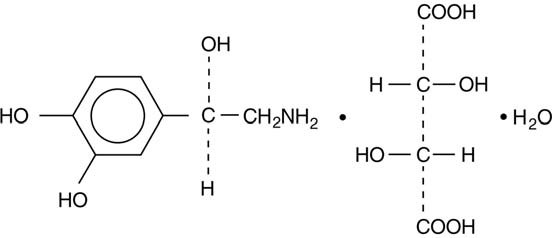 DRUG LABEL: NOREPINEPHRINE BITARTRATE IN SODIUM CHLORIDE
NDC: 44567-640 | Form: INJECTION, SOLUTION
Manufacturer: WG Critical Care, LLC
Category: prescription | Type: HUMAN PRESCRIPTION DRUG LABEL
Date: 20260217

ACTIVE INGREDIENTS: NOREPINEPHRINE BITARTRATE 0.016 mg/1 mL
INACTIVE INGREDIENTS: SODIUM CHLORIDE; HYDROCHLORIC ACID; SODIUM HYDROXIDE

HIGHLIGHTS OF PRESCRIBING INFORMATION

These highlights do not include all the information needed to use NOREPINEPHRINE BITARTRATE IN SODIUM CHLORIDE INJECTION safely and effectively. See full prescribing information for NOREPINEPHRINE BITARTRATE IN SODIUM CHLORIDE INJECTION.
NOREPINEPHRINE BITARTRATE IN SODIUM CHLORIDE injection, for intravenous use
Initial U.S. Approval: 1950

1 INDICATIONS AND USAGE

Norepinephrine Bitartrate in Sodium Chloride Injection is a catecholamine indicated for restoration of blood pressure in adult patients with acute hypotensive states. (1)

2 DOSAGE AND ADMINISTRATION

- Initiate 8 to 12 mcg/min and adjust the rate to maintain blood pressure sufficient to maintain the circulation of vital organs. (2.2)
- The average maintenance dose ranges from 2 to 4 mcg/min. (2.2)

3 DOSAGE FORMS AND STRENGTHS

Injection:

- 4 mg/250 mL (16 mcg per mL) of norepinephrine, single-dose bags (3)
- 8 mg/250 mL (32 mcg per mL) of norepinephrine, single-dose bags. (3)
- 16 mg/250 mL (64 mcg per mL) of norepinephrine, single-dose bags (3)
- 32 mg/250 mL (128 mcg per mL) of norepinephrine, single-dose bags (3)

4 CONTRAINDICATIONS

None. (4)

5 WARNINGS AND PRECAUTIONS

- Tissue Ischemia: Avoid extravasation into tissues, which can cause local necrosis. (5.1)
- Hypotension After Abrupt Discontinuation: Sudden cessation of the infusion rate may result in marked hypotension. Reduce the Norepinephrine Bitartrate in Sodium Chloride Injection infusion rate gradually. (5.2)
- Cardiac Arrhythmias: Norepinephrine Bitartrate in Sodium Chloride Injection may cause arrhythmias. Monitor cardiac function in patients with underlying heart disease. (5.3)

6 ADVERSE REACTIONS

Most common adverse reactions are ischemic injury, bradycardia, anxiety, transient headache, respiratory difficulty, and extravasation necrosis at injection site. (6)

To report SUSPECTED ADVERSE REACTIONS, contact WG Critical Care, LLC at 1-866-562-4708, or FDA at 1-800-FDA-1088 or www.fda.gov/medwatch.

7 DRUG INTERACTIONS

- Monoamine oxidase inhibitors (MAOI) or tricyclic antidepressants of the triptyline or imipramine types may result in hypertension. (7.1, 7.2)
- Antidiabetics: Norepinephrine can decrease insulin sensitivity and raise blood glucose. (7.3)
- Cyclopropane and halothane anesthetics increase cardiac autonomic irritability. (7.4)

8 USE IN SPECIFIC POPULATIONS

- Elderly patients may be at greater risk of developing adverse reactions. (8.5)

FULL PRESCRIBING INFORMATION

1 INDICATIONS AND USAGE

Norepinephrine Bitartrate in Sodium Chloride Injection is indicated to raise blood pressure in adult patients with severe, acute hypotension.

2 DOSAGE AND ADMINISTRATION

2.1 Important Dosage and Administration Instructions

Correct Hypovolemia

Address hypovolemia before initiation of Norepinephrine Bitartrate in Sodium Chloride Injection therapy. If the patient does not respond to therapy, suspect occult hypovolemia [see Warnings and Precautions (5.1)].

Administration

Norepinephrine Bitartrate in Sodium Chloride Injection is a ready to administer product that requires no further dilution prior to infusion. Parenteral drug products should be inspected visually for particulate matter and discoloration prior to administration, whenever solution and container permit.

Infuse Norepinephrine Bitartrate in Sodium Chloride Injection into a large vein. Avoid infusions into the veins of the leg in the elderly or in patients with occlusive vascular disease of the legs [see Warnings and Precautions (5.1)]. Avoid using a catheter-tie-in technique.

Discontinuation

When discontinuing the infusion, reduce the flow rate gradually. Avoid abrupt withdrawal. Discard unused portion.

2.2 Dosage

After an initial dosage of 8 to 12 mcg per minute via intravenous infusion, assess patient response and adjust dosage to maintain desired hemodynamic effect. Monitor blood pressure every two minutes until the desired hemodynamic effect is achieved, and then monitor blood pressure every five minutes for the duration of the infusion.

Typical maintenance intravenous dosage is 2 to 4 mcg per minute.

2.4 Drug Incompatibilities

Avoid contact with iron salts, alkalis, or oxidizing agents.

Whole blood or plasma, if indicated to increase blood volume, should be administered separately.

3 DOSAGE FORMS AND STRENGTHS

Injection:

Norepinephrine Bitartrate in Sodium Chloride is a clear, colorless solution, available as:

- 4 mg/250 mL (16 mcg per mL) of norepinephrine (free base), single-dose bags
- 8 mg/250 mL (32 mcg per mL) of norepinephrine (free base), single-dose bags
- 16 mg/250 mL (64 mcg per mL) of norepinephrine (free base), single-dose bags
- 32 mg/250 mL (128 mcg per mL) of norepinephrine (free base), single-dose bags

4 CONTRAINDICATIONS

None.

5 WARNINGS AND PRECAUTIONS

5.1 Tissue Ischemia

Administration of Norepinephrine Bitartrate in Sodium Chloride Injection to patients who are hypotensive from hypovolemia can result in severe peripheral and visceral vasoconstriction, decreased renal perfusion and reduced urine output, tissue hypoxia, lactic acidosis, and reduced systemic blood flow despite "normal" blood pressure. Address hypovolemia prior to initiating Norepinephrine Bitartrate in Sodium Chloride Injection [see Dosage and Administration (2.1)]. Avoid Norepinephrine Bitartrate in Sodium Chloride Injection in patients with mesenteric or peripheral vascular thrombosis, as this may increase ischemia and extend the area of infarction.

Gangrene of the extremities has occurred in patients with occlusive or thrombotic vascular disease or who received prolonged or high dose infusions. Monitor for changes to the skin of the extremities in susceptible patients.

Extravasation of Norepinephrine Bitartrate in Sodium Chloride Injection may cause necrosis and sloughing of surrounding tissue. To reduce the risk of extravasation, infuse into a large vein, check the infusion site frequently for free flow, and monitor for signs of extravasation [see Dosage and Administration (2.1)].

Emergency Treatment of Extravasation

To prevent sloughing and necrosis in areas in which extravasation has occurred, infiltrate the ischemic area as soon as possible, using a syringe with a fine hypodermic needle with 5 to 10 mg of phentolamine mesylate in 10 to 15 mL of 0.9% Sodium Chloride Injection in adults.

Sympathetic blockade with phentolamine causes immediate and conspicuous local hyperemic changes if the area is infiltrated within 12 hours.

5.2 Hypotension after Abrupt Discontinuation

Sudden cessation of the infusion rate may result in marked hypotension. When discontinuing the infusion, gradually reduce the Norepinephrine Bitartrate in Sodium Chloride Injection infusion rate while expanding blood volume with intravenous fluids.

5.3 Cardiac Arrhythmias

Norepinephrine Bitartrate in Sodium Chloride Injection elevates intracellular calcium concentrations and may cause arrhythmias, particularly in the setting of hypoxia or hypercarbia. Perform continuous cardiac monitoring of patients with arrhythmias.

6 ADVERSE REACTIONS

The following adverse reactions are described in greater detail in other sections:

- Tissue Ischemia [see Warnings and Precautions (5.1)]
- Hypotension [see Warnings and Precautions (5.2)]
- Cardiac Arrhythmias [see Warnings and Precautions (5.3)]

The most common adverse reactions are hypertension and bradycardia.

The following adverse reactions can occur:

Nervous system disorders: Anxiety, headache

Respiratory disorders: Respiratory difficulty, pulmonary edema

7 DRUG INTERACTIONS

7.1 MAO-Inhibiting Drugs

Co-administration of Norepinephrine Bitartrate in Sodium Chloride Injection with monoamine oxidase (MAO) inhibitors or other drugs with MAO-inhibiting properties (e.g., linezolid) can cause severe, prolonged hypertension.

If administration of Norepinephrine Bitartrate in Sodium Chloride Injection cannot be avoided in patients who recently have received any of these drugs and in whom, after discontinuation, MAO activity has not yet sufficiently recovered, monitor for hypertension.

7.2 Tricyclic Antidepressants

Co-administration of Norepinephrine Bitartrate in Sodium Chloride Injection with tricyclic antidepressants (including amitriptyline, nortriptyline, protriptyline, clomipramine, desipramine, imipramine) can cause severe, prolonged hypertension. If administration of Norepinephrine Bitartrate in Sodium Chloride Injection cannot be avoided in these patients, monitor for hypertension.

7.3 Antidiabetics

Norepinephrine Bitartrate in Sodium Chloride Injection can decrease insulin sensitivity and raise blood glucose. Monitor glucose and consider dosage adjustment of antidiabetic drugs.

7.4 Halogenated Anesthetics

Concomitant use of Norepinephrine Bitartrate in Sodium Chloride Injection with halogenated anesthetics (e.g., cyclopropane, desflurane, enflurane, isoflurane, and sevoflurane) may lead to ventricular tachycardia or ventricular fibrillation. Monitor cardiac rhythm in patients receiving concomitant halogenated anesthetics.

8 USE IN SPECIFIC POPULATIONS

8.1 Pregnancy

Risk Summary

Limited published data consisting of a small number of case reports and multiple small trials involving the use of norepinephrine in pregnant women at the time of delivery have not identified an increased risk of major birth defects, miscarriage or adverse maternal or fetal outcomes. There are risks to the mother and fetus from hypotension associated with septic shock, myocardial infarction and stroke which are medical emergencies in pregnancy and can be fatal if left untreated. (see Clinical Considerations). In animal reproduction studies, using high doses of intravenous norepinephrine resulted in lowered maternal placental blood flow. Clinical relevance to changes in the human fetus is unknown since the average maintenance dose is ten times lower (see Data). Increased fetal reabsorptions were observed in pregnant hamsters after receiving daily injections at approximately 2 times the maximum recommended dose on a mg/m^3 basis for four days during organogenesis (see Data).

The estimated background risk for major birth defects and miscarriage for the indicated population is unknown. All pregnancies have a background risk of birth defect, loss, or other adverse outcomes. In the U.S. general population, the estimated background risk of major birth defects and miscarriage in the clinically recognized pregnancies is 2–4% and 15–20%, respectively.

Clinical Considerations

Disease-associated maternal and/or embryo/fetal risk

Hypotension associated with septic shock, myocardial infarction, and stroke are medical emergencies in pregnancy which can be fatal if left untreated. Delaying treatment in pregnant women with hypotension associated with septic shock, myocardial infarction and stroke may increase the risk of maternal and fetal morbidity and mortality. Life-sustaining therapy for the pregnant woman should not be withheld due to potential concerns regarding the effects of norepinephrine on the fetus.

Data

Animal Data

A study in pregnant sheep receiving high doses of intravenous norepinephrine (40 mcg/min, at approximately 10 times the average maintenance dose of 2–4 mcg/min in human, on a mg/kg basis) exhibited a significant decrease in maternal placental blood flow. Decreases in fetal oxygenation, urine and lung liquid flow were also observed.

Norepinephrine administration to pregnant rats on Gestation Day 16 or 17 resulted in cataract production in rat fetuses.

In hamsters, an increased number of resorptions (29.1% in study group vs. 3.4% in control group), fetal microscopic liver abnormalities and delayed skeletal ossification were observed at approximately 2 times the maximum recommended intramuscular or subcutaneous dose (on a mg/m^2 basis at a maternal subcutaneous dose of 0.5 mg/kg/day from Gestation Day 7–10).

8.2 Lactation

Risk Summary

There are no data on the presence of norepinephrine in either human or animal milk, the effects on the breastfed infant, or the effects on milk production. Clinically relevant exposure to the infant is not expected based on the short half-life and poor oral bioavailability of norepinephrine.

8.4 Pediatric Use

Safety and effectiveness in pediatric patients have not been established.

8.5 Geriatric Use

Clinical studies of Norepinephrine Bitartrate in Sodium Chloride Injection did not include sufficient numbers of subjects aged 65 and over to determine whether they respond differently from younger subjects. Other reported clinical experience has not identified differences in responses between the elderly and younger patients. In general, dose selection for an elderly patient should be cautious, usually starting at the low end of the dosing range, reflecting the greater frequency of decreased hepatic, renal, or cardiac function, and of concomitant disease or other drug therapy.

Avoid administration of Norepinephrine Bitartrate in Sodium Chloride Injection into the veins in the leg in elderly patients [see Warnings and Precautions (5.1)].

10 OVERDOSAGE

Overdosage with Norepinephrine Bitartrate in Sodium Chloride Injection may result in headache, severe hypertension, reflex bradycardia, marked increase in peripheral resistance, and decreased cardiac output.

In case of overdosage, discontinue Norepinephrine Bitartrate in Sodium Chloride Injection until the condition of the patient stabilizes.

11 DESCRIPTION

Norepinephrine Bitartrate in Sodium Chloride Injection contains the active pharmaceutical ingredient norepinephrine, a catecholamine, in the form of bitartrate salt (monohydrate). Norepinephrine is sometimes referred to as l-arterenol/Levarterenol or l-norepinephrine which differs from epinephrine by the absence of a methyl group on the nitrogen atom.

The chemical name for norepinephrine bitartrate (monohydrate) is (-)-α-(aminomethyl)-3,4-dihydroxybenzyl alcohol tartrate (1:1) (salt) monohydrate (molecular weight 337.3 g/mol) and has the following structural formula:

Norepinephrine bitartrate (monohydrate) is sparingly soluble in water, very slightly soluble in alcohol and ether, and readily soluble in acids.

Norepinephrine Bitartrate in 0.9% Sodium Chloride Injection is supplied as a sterile aqueous ready-to-use solution in 250 mL transparent intravenous bags. Each mL contains 32 mcg, 64 mcg, 128 mcg or 256 mcg of norepinephrine bitartrate monohydrate, equivalent to 16 mcg, 32 mcg, 64 mcg or 128 mcg of norepinephrine base, respectively. Each mL also contains 9 mg of Sodium Chloride USP as a tonicity agent, and may contain Hydrochloric Acid NF and Sodium Hydroxide NF as pH adjusters, for a pH range of 3.4 to 4.0, in Water for Injection.

12 CLINICAL PHARMACOLOGY

12.1 Mechanism of Action

Norepinephrine is a peripheral vasoconstrictor (alpha-adrenergic action) and an inotropic stimulator of the heart and dilator of coronary arteries (beta-adrenergic action).

12.2 Pharmacodynamics

The primary pharmacodynamic effects of norepinephrine are cardiac stimulation and vasoconstriction. Cardiac output is generally unaffected, although it can be decreased, and total peripheral resistance is also elevated. The elevation in resistance and pressure result in reflex vagal activity, which slows the heart rate and increases stroke volume. The elevation in vascular tone or resistance reduces blood flow to the major abdominal organs as well as to skeletal muscle. Coronary blood flow is substantially increased secondary to the indirect effects of alpha stimulation. After intravenous administration, a pressor response occurs rapidly and reaches steady state within 5 minutes. The pharmacologic actions of norepinephrine are terminated primarily by uptake and metabolism in sympathetic nerve endings. The pressor action stops within 1–2 minutes after the infusion is discontinued.

12.3 Pharmacokinetics

Absorption

Following initiation of intravenous infusion, the steady state plasma concentration is achieved in 5 min.

Distribution

Plasma protein binding of norepinephrine is approximately 25%. It is mainly bound to plasma albumin and to a smaller extent to prealbumin and alpha 1-acid glycoprotein. The volume of distribution is 8.8 L. Norepinephrine localizes mainly in sympathetic nervous tissue. It crosses the placenta but not the blood-brain barrier.

Elimination

The mean half-life of norepinephrine is approximately 2.4 min. The average metabolic clearance is 3.1 L/min.

Metabolism

Norepinephrine is metabolized in the liver and other tissues by a combination of reactions involving the enzymes catechol-O-methyltransferase (COMT) and MAO. The major metabolites are normetanephrine and 3-methoxyl-4-hydroxy mandelic acid (vanillylmandelic acid, VMA), both of which are inactive. Other inactive metabolites include 3-methoxy-4-hydroxyphenylglycol, 3,4-dihydroxymandelic acid, and 3,4-dihydroxyphenylglycol.

Excretion

Noradrenaline metabolites are excreted in urine primarily as sulphate conjugates and, to a lesser extent, as glucuronide conjugates. Only small quantities of norepinephrine are excreted unchanged.

13 NONCLINICAL TOXICOLOGY

13.1 Carcinogenesis, Mutagenesis, Impairment of Fertility

Carcinogenesis, mutagenesis, and fertility studies have not been performed.

16 HOW SUPPLIED/STORAGE AND HANDLING

Norepinephrine Bitartrate in Sodium Chloride Injection, is a clear, colorless solution, filled in 250 mL single-dose transparent intravenous Nexcel bags as:

NDC Configuration | Packaging Configuration | Total Norepinephrine Bitartrate
44567-640-01 | 1 single-dose bag | 4 mg per 250 mL (16 mcg per mL)
44567-640-10 | 10 bags per carton | 4 mg per 250 mL (16 mcg per mL)
44567-641-01 | 1 single-dose bag | 8 mg per 250 mL (32 mcg per mL)
44567-641-10 | 10 bags per carton | 8 mg per 250 mL (32 mcg per mL)
44567-642-01 | 1 single-dose bag | 16 mg per 250 mL (64 mcg per mL)
44567-642-10 | 10 bags per carton | 16 mg per 250 mL (64 mcg per mL)
44567-643-01 | 1 single-dose bag | 32 mg per 250 mL (128 mcg per mL)
44567-643-10 | 10 bags per carton | 32 mg per 250 mL (128 mcg per mL)

Each filled bag is packed in an overwrap with a transparent band and oxygen absorber and oxygen indicator placed inside the overwrapping to prevent deterioration of drug product. Product should be used within 7 days of removal from overwrap.

Do not use the product if the oxygen indicator has changed color to green or blue before opening the overwrap. Normal color is yellow or orange.

Store at 20°C to 25°C (68°F to 77°F) [see USP Controlled Room Temperature] in the original carton to protect from light. Do not freeze.

17 PATIENT COUNSELING INFORMATION

Risk of Tissue Damage

Advise the patient, family, or caregiver to report signs of extravasation urgently [see Warnings and Precautions (5.1)].

Manufactured for:

WG Critical Care, LLC

Paramus, NJ 07652

Made in Switzerland

Patents: www.wgcriticalcare.com/injectable-pharmaceuticals/about-us/patents/

Package/Label Display Panel

NDC 44567-640-01

Norepinephrine Bitartrate in 0.9% Sodium Chloride Injection

4 mg per 250 mL (16 mcg per mL)

Package/Label Display Panel

NDC 44567-641-01

Norepinephrine Bitartrate in 0.9% Sodium Chloride Injection

8 mg per 250 mL (32 mcg per mL)

Package/Label Display Panel

NDC 44567-642-01

Norepinephrine Bitartrate in 0.9% Sodium Chloride Injection

16 mg per 250 mL (64 mcg per mL)

Package/Label Display Panel

NDC 44567-643-01

Norepinephrine Bitartrate in 0.9% Sodium Chloride Injection

32 mg per 250 mL (128 mcg per mL)